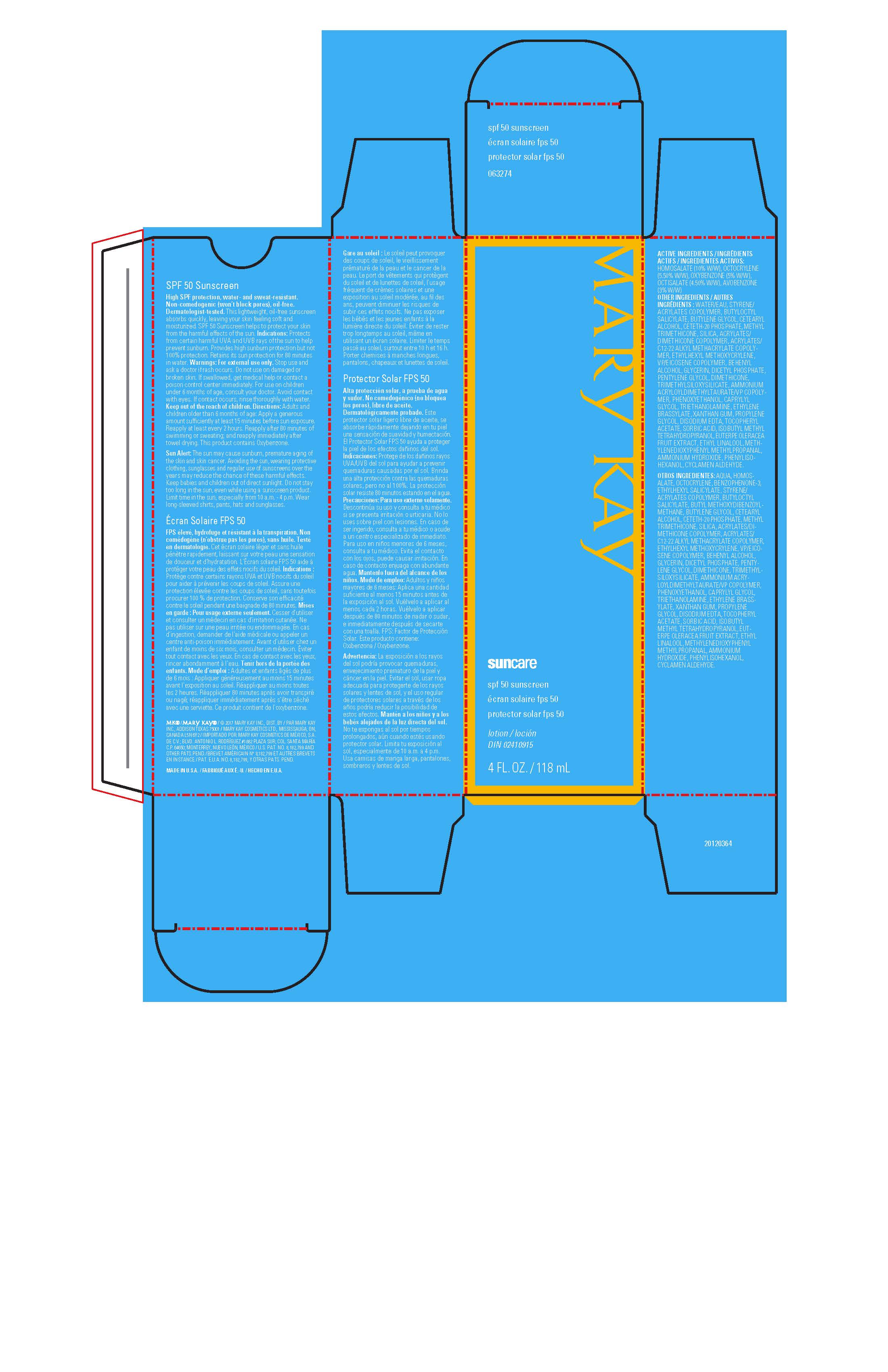 DRUG LABEL: Mary Kay Suncare SPF 50 Sunscreen
NDC: 51531-3274 | Form: LOTION
Manufacturer: Mary Kay Inc.
Category: otc | Type: HUMAN OTC DRUG LABEL
Date: 20241217

ACTIVE INGREDIENTS: AVOBENZONE 3 g/100 mL; HOMOSALATE 10 g/100 mL; OCTISALATE 4.5 g/100 mL; OCTOCRYLENE 5.5 g/100 mL; OXYBENZONE 5 g/100 mL
INACTIVE INGREDIENTS: PROPYLENE GLYCOL; EDETATE DISODIUM; .ALPHA.-TOCOPHEROL ACETATE; SORBIC ACID; 2-ISOBUTYL-4-METHYLTETRAHYDROPYRAN-4-OL; 3-(3,4-METHYLENEDIOXYPHENYL)-2-METHYLPROPANAL; ACAI; ETHYL LINALOOL; AMMONIA; PHENYLISOHEXANOL; CYCLAMEN ALDEHYDE; TROLAMINE; ETHYLENE BRASSYLATE; XANTHAN GUM; WATER; BUTYLOCTYL SALICYLATE; BUTYLENE GLYCOL; CETOSTEARYL ALCOHOL; CETETH-20 PHOSPHATE; METHYL TRIMETHICONE; SILICON DIOXIDE; DOCOSANOL; ETHYLHEXYL METHOXYCRYLENE; GLYCERIN; DIHEXADECYL PHOSPHATE; PENTYLENE GLYCOL; TRIMETHYLSILOXYSILICATE (M/Q 0.6-0.8); DIMETHICONE; AMMONIUM ACRYLOYLDIMETHYLTAURATE/VP COPOLYMER; PHENOXYETHANOL; VINYLPYRROLIDONE/EICOSENE COPOLYMER; CAPRYLYL GLYCOL

Mary Kay Suncare Sunscreen SPF 50 CA/LATAM Export Only

ACTIVE INGREDIENTS:

HOMOSALATE (10% W/W)

OCTOCRYLENE (5.50% W/W)

OXYBENZONE (5% W/W)

OCTISALATE (4.50% W/W)

AVOBENZONE (3% W/W)

Indications:

Protects from certain harmful UVA and UVB rays of the sun to help prevent sunburn.

Provides high sunburn protection but not 100% protection.

Retains its sun protection for 80 minutes in water.

Warnings:

For external use only.

Stop use and ask a doctor if rash occurs .

Do not use on damaged or broken skin.

If swallowed, get medical help or contact a poison control center immediately.

For use on children under 6 months of age, consult your doctor.

Avoid contact with eyes.

If contact occurs, rinse thoroughly with water.

Keep out of reach of children.

Sun Alert: The sun may cause sunburn, premature aging of the skin and skin cancer.

Avoiding the sun, wearing protective clothing, sunglasses, and regular use of sunscreens over the years may reduce the chance of these harmful effects.

Keep babies and children out of direct sunlight.

Do not stay too long in the sun, even while using a sunscreen product.

Limit time in the sun, especially from 10 a.m. - 4 p.m.).

Wear long-sleeved shirts, pants, hats and sunglasses.

This product contains Oxybenzone.

Directions:

Adults and children older than 6 months of age: Apply a generous amount sufficiently at least 15 minutes before sun exposure.

Reapply at least every 2 hours.

Reapply after 80 minutes of swimming or sweating, and reapply immediately after towel drying.

Ingredients:

WATER/EAU, STYRENE/ACRYLATES COPOLYMER, BUTYLOCTYL SALICYLATE,

BUTYLENE GLYCOL, CETEARYL ALCOHOL, CETETH-20 PHOSPHATE, METHYL TRIMETHICONE,

SILICA, ACRYLATES/DIMETHICONE COPOLYMER, ACRYLATES/C12-22 ALKYL METHACRYLATE COPOLYMER,

ETHYLHEXYL METHOXYCRYLENE, VP/EICOSENE COPOLYMER, BEHENYL ALCOHOL, GLYCERIN,

DICETYL PHOSPHATE, PENTYLENE GLYCOL, DIMETHICONE, TRIMETHYLSILOXYSILICATE,

AMMONIUM ACRYLOYLDIMETHYLTAURATE/VP COPOLYMER, PHENOXYETHANOL, CAPRYLYL GLYCOL,

TRIETHANOLAMINE, ETHYLENE BRASSYLATE, XANTHAN GUM, PROPYLENE GLYCOL, DISODIUM EDTA,

TOCOPHERYL ACETATE, SORBIC ACID, ISOBUTYL METHYL TETRAHYDROPYRANOL,

EUTERPE OLERACEA FRUIT EXTRACT, ETHYL LINALOOL, METHYLENEDIOXYPHENYL METHYLPROPANAL,

AMMONIUM HYDROXIDE, PHENYLISOHEXANOL, CYCLAMEN ALDEHYDE.

Principal Display Panel - 118 mL carton

Mary Kay

suncare

spf 50 sunscreen

écran solaire fps 50

protector solar fps 50

lotion/loción

DIN 02410915

4 FL. OZ. / 118 mL